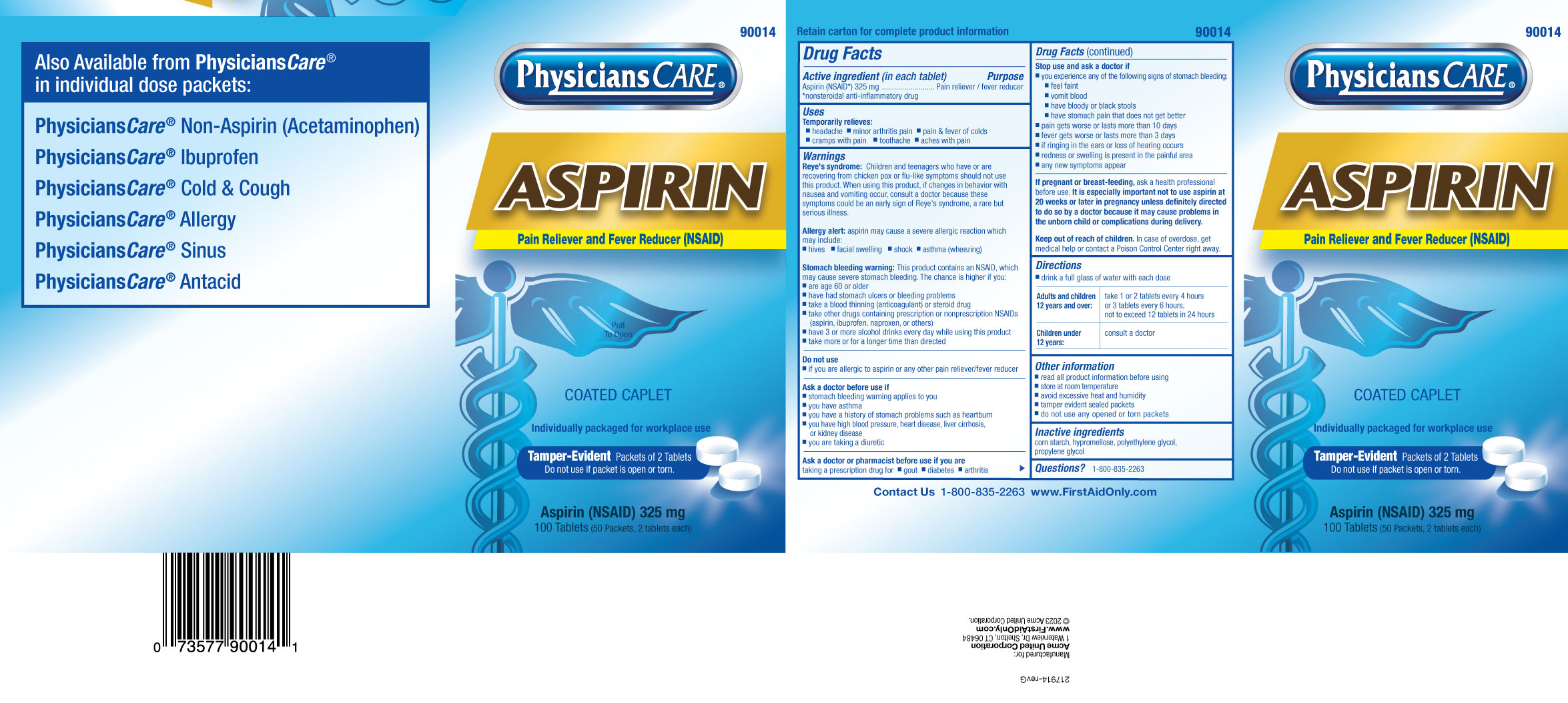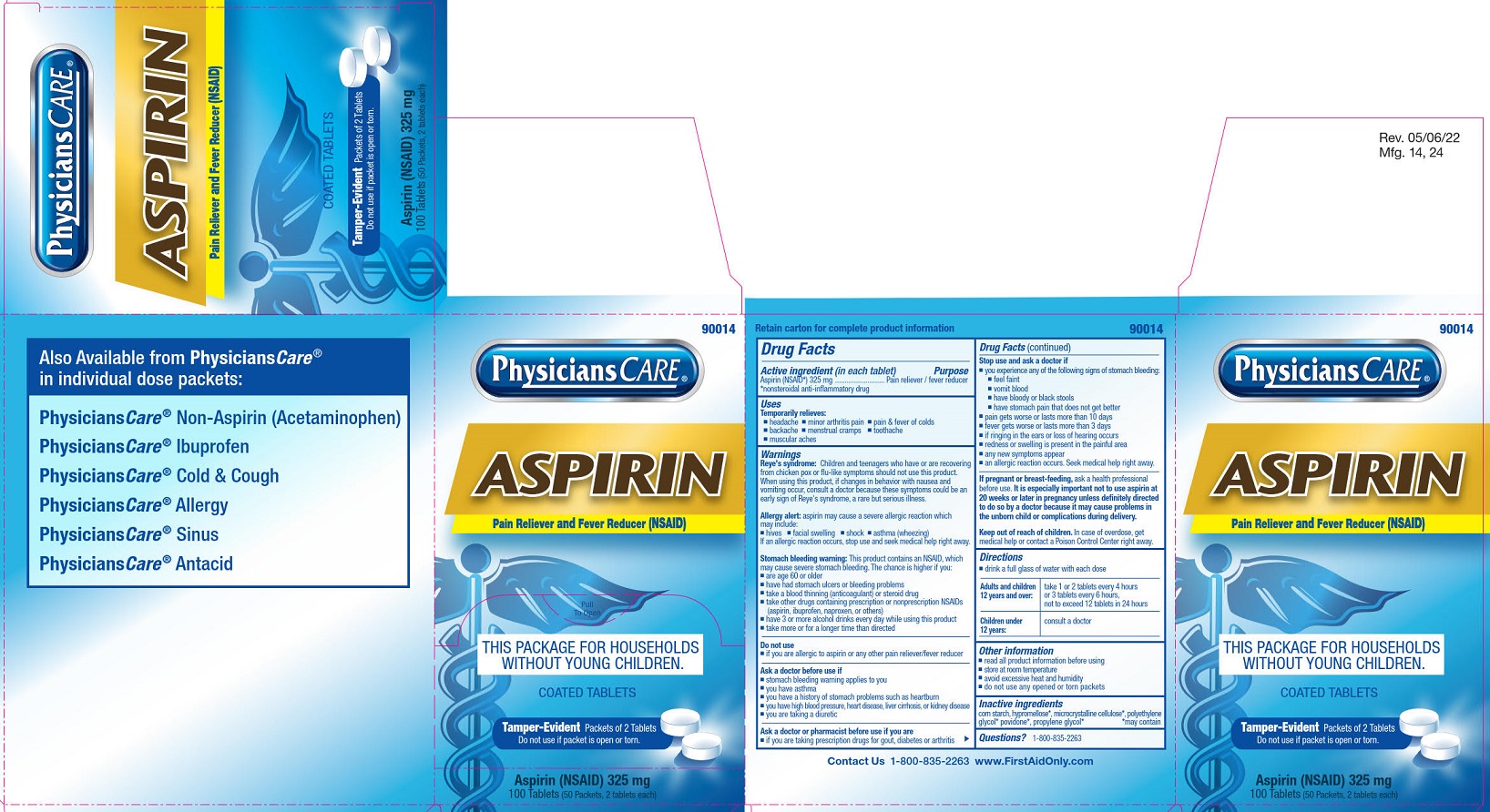 DRUG LABEL: Physicians Care Aspirin
NDC: 0924-0106 | Form: TABLET, COATED
Manufacturer: Acme United Corporation
Category: otc | Type: HUMAN OTC DRUG LABEL
Date: 20251031

ACTIVE INGREDIENTS: ASPIRIN 325 mg/1 1
INACTIVE INGREDIENTS: STARCH, CORN; CELLULOSE, MICROCRYSTALLINE; POVIDONE

Physicians Care Aspirin

Drug Facts

Active ingredient (in each tablet)

Aspirin (NSAID*) 325 mg

*nonsteroidal anti-inflammatory drug

Purpose

Pain reliever/fever reducer

Uses

Temporarily relieves:

■ headache

■ minor arthritis pain

■ pain & fever of colds

■ backache

■ menstrual cramps

■ toothache

■ muscle aches

Warnings

Reye's syndrome: Children and teenagers who have or are recovering from chicken pox or flu-like symptoms should not use this product. When using this product, if changes in behavior with nausea and vomiting occur, consult a doctor because these symptoms could be an early sign of Reye's syndrome, a rare but serious illness.

Allergy alert: Aspirin may cause a severe allergic reaction which may include:

■ hives

■ facial swelling

■ shock

■ asthma (wheezing)

If an allergic reaction occurs, stop use and seek medical help right away.

Stomach bleeding warning: This product contains an NSAID, which may cause severe stomach bleeding. The chance is higher if you:

■ are age 60 or older

■ have had stomach ulcers or bleeding problems

■ take a blood thinning (anticoagulant) or steroid drug

■ take other drugs containing prescription or nonprescription NSAIDs (aspirin, ibuprofen, naproxen, or others)

■ have 3 or more alcohol drinks every day while using this product

■ take more or for a longer time than directed

Do not use

■ if you are allergic to aspirin or to any other pain reliever/fever reducer

Ask a doctor before use if

■ stomach bleeding warning applies to you

■ you have asthma

■ you have a history of stomach problems such as heartburn

■ you have high blood pressure, heart disease, liver cirrhosis, or kidney disease

■ you are taking a diuretic

Ask a doctor or pharmacist before use if you are

■ taking prescription drugs for gout, diabetes or arthritis

Stop use and ask a doctor if

■ you experience any of the following signs of stomach bleeding:

■ feel faint ■ vomit blood ■ have bloody or black stools ■ have stomach pain that does not get better

■ pain gets worse or lasts more than 10 days

■ fever gets worse or lasts more than 3 days

■ if ringing in the ears or loss of hearing occurs

■ redness or swelling is present in the painful area

■ any new symptoms appear

■ an allergic reaction occurs. Seek medical help right away.

PREGNANCY OR BREAST FEEDING

If pregnant or breast-feeding,ask a health professional before use. It is especially important not to use aspirin at 20 weeks or later in pregnancy unless specifically directed to do so by a doctor because it may cause problems in the unborn child or complications during delivery.

Keep out of reach of children. In case of overdose, get medical help or contact a Poison Control Center right away.

Directions

■ drink a full glass of water with each dose

Adults and children 12 years and over:

take 1 or 2 tablets every 4 hours or 3 tablets every 6 hours, not to exceed 12 tablets in 24 hours

Children under 12 years:

consult a doctor

Other information

■ read all product information before using

■ store at room temperature

■ avoid excessive heat and humidity

■ do not use any opened or torn packets

Inactive ingredients

corn starch, hypromellose, polyethylene glycol, propylene glycol

Questions or comments? 1-800-835-2263

Physicians Care Aspirin Label

90014

Physicians Care®

Aspirin

Pain Reliever and fever Reducer (NSAID)

Pull To Open

This Package for Households without Young Children.

Coated Tablets

Tamper-Evident Packets of 2 Tablets

Do not use if packet is open or torn.

Aspirin (NSAID) 325 mg

100 Tablets (50 Packets, 2 tablets each)

PACKAGE LABEL

90014

Physicians Care®

Aspirin

Pain Reliever and fever Reducer (NSAID)

Pull To Open

This Package for Households without Young Children.

Coated Tablets

Tamper-Evident Packets of 2 Tablets

Do not use if packet is open or torn.

Aspirin (NSAID) 325 mg

100 Tablets (50 Packets, 2 tablets each)